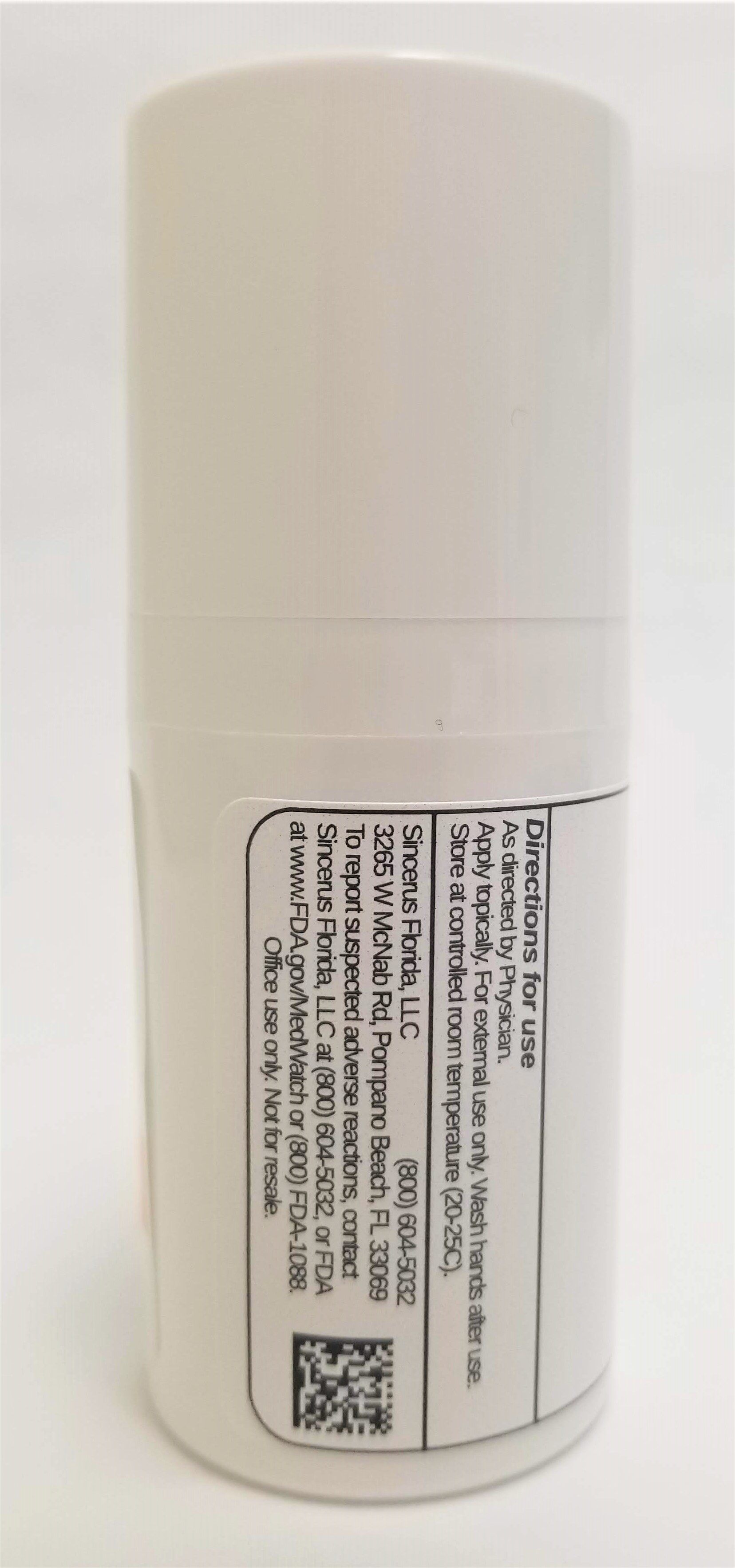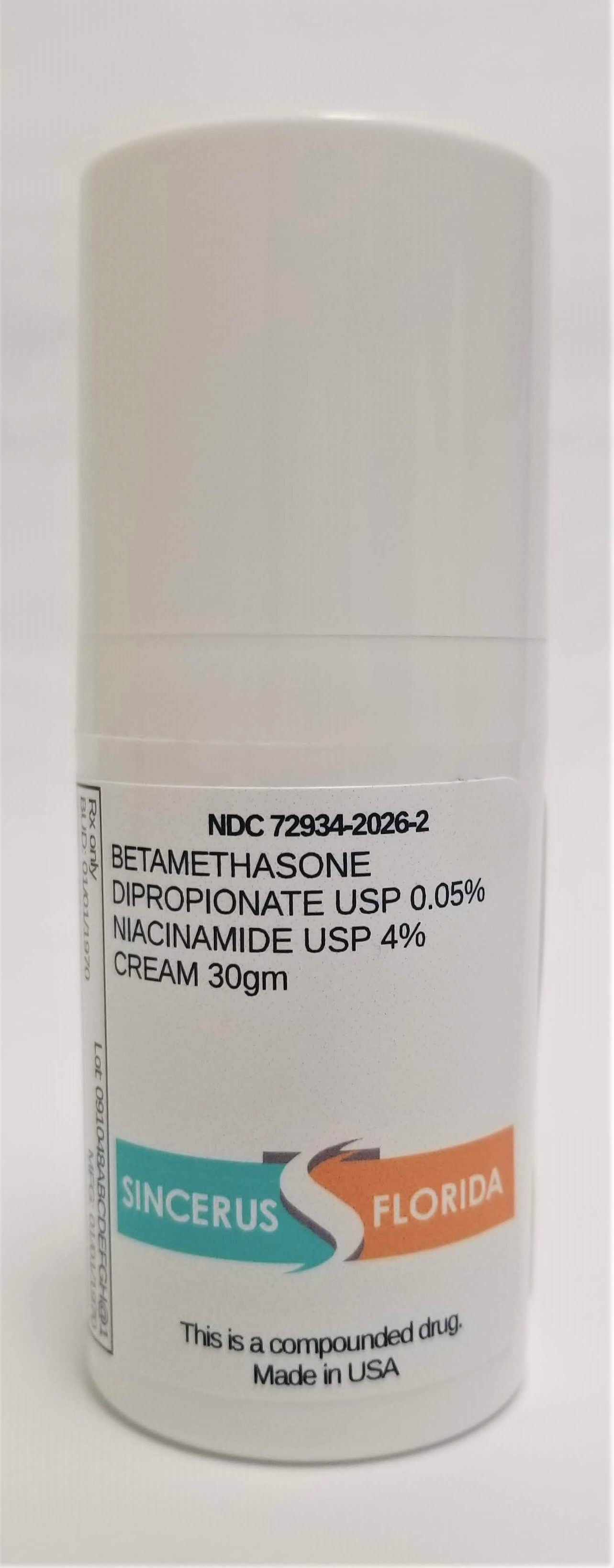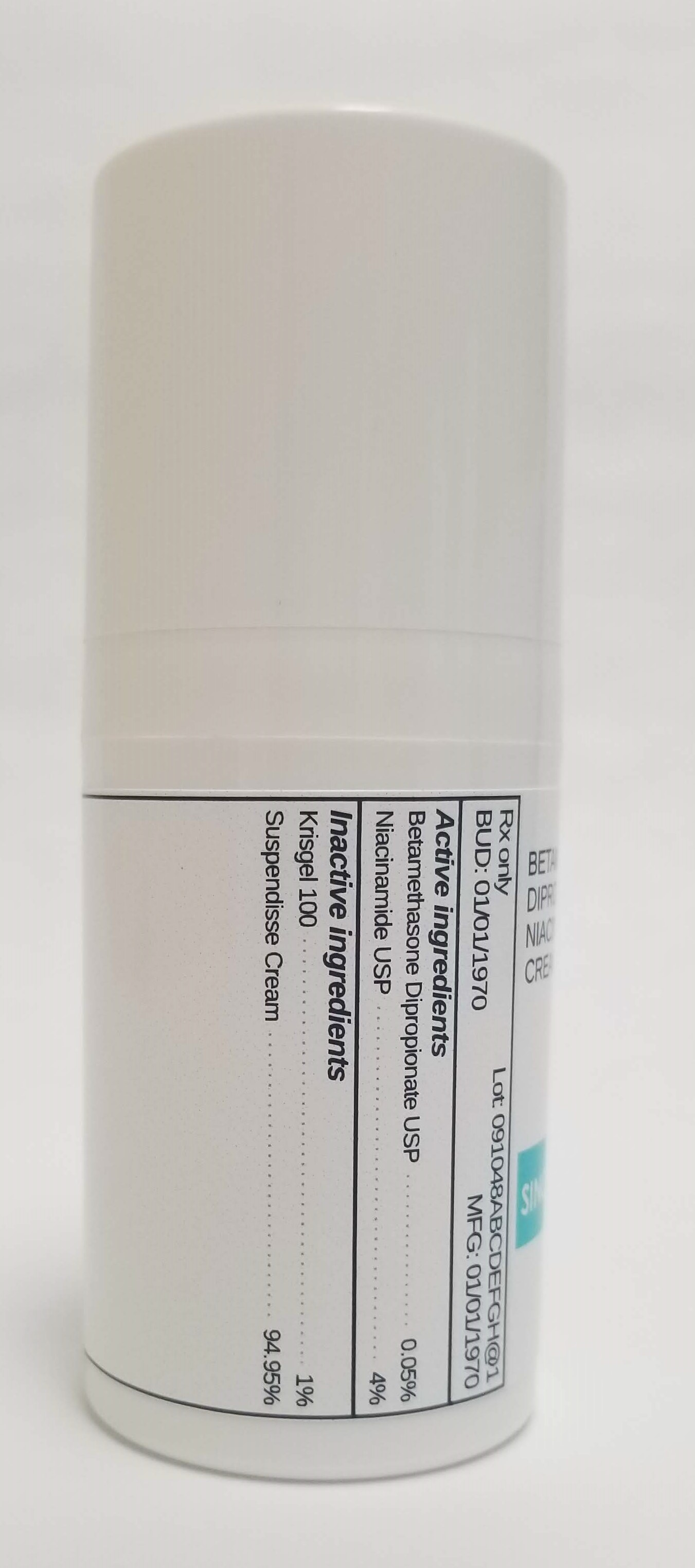 DRUG LABEL: BETAMETHASONE  DIPROPIONATE 0.05% / NIACINAMIDE 4%
NDC: 72934-2026 | Form: CREAM
Manufacturer: Sincerus Florida, LLC
Category: prescription | Type: HUMAN PRESCRIPTION DRUG LABEL
Date: 20190520

ACTIVE INGREDIENTS: BETAMETHASONE DIPROPIONATE 0.05 g/100 g; NIACINAMIDE 4 g/100 g

BETAMETHASONE DIPROPIONATE 0.05% / NIACINAMIDE 4%